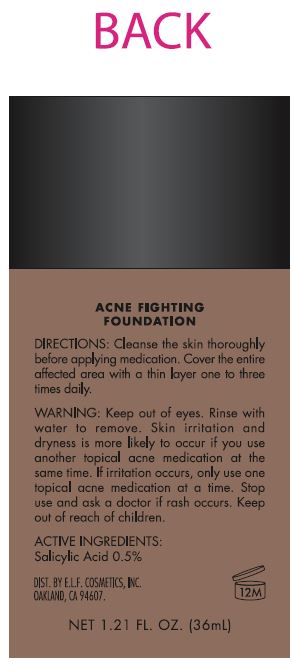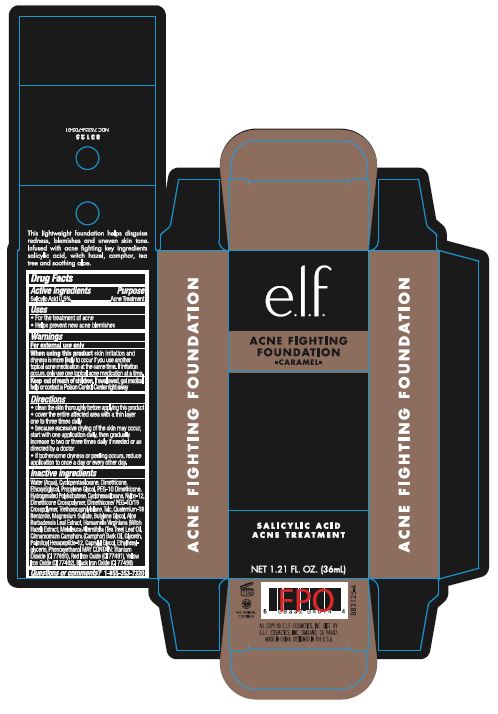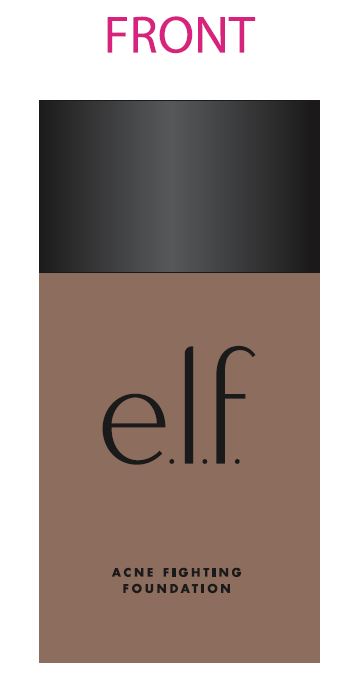 DRUG LABEL: ELF ACNE Fighting Foundation Caramel
NDC: 76354-705 | Form: CREAM
Manufacturer: e.l.f. Cosmetics, Inc
Category: otc | Type: HUMAN OTC DRUG LABEL
Date: 20241212

ACTIVE INGREDIENTS: SALICYLIC ACID 0.5 g/100 mL
INACTIVE INGREDIENTS: HYDROGENATED POLYBUTENE (1300 MW); WATER; DIMETHICONE; CAMPHOR OIL; DIMETHICONE PEG-10 PHOSPHATE; PROPYLENE GLYCOL; NYLON-12; TALC; PHENOXYETHANOL; FERRIC OXIDE RED; FERRIC OXIDE YELLOW; FERROSOFERRIC OXIDE; TITANIUM DIOXIDE; MAGNESIUM SULFATE ANHYDROUS; TRIETHOXYCAPRYLYLSILANE; METHYLPARABEN; ETHYLPARABEN; PROPYLPARABEN; BUTYLPARABEN; ISOBUTYLPARABEN; TEA TREE OIL; ALOE VERA LEAF; WITCH HAZEL

ELF ACNE Fighting Foundation Caramel

Active Ingredient:

Salicylic Acid 0.5%

Purpose:

Acne Treatment

Uses:

For the treatment of acne

Helps prevent new acne blemishes

Warning:

For external use only

When Using This Product:

Keep out of eyes, rinse with water to remove.

Skin irrittion and dryness is more likely to occur if you use another topical acne medications at the same time. If irritation occurs, only use one medication at a time.

Stop use and ask a doctor If

rash occurs

Keep Out of Reach of Children

Directions:

Cleanse the skin thoroughly before applying medication. Cover the entire affected area with a thin layer one to three times daily. Because excessive drying of skin may occur, start with one application daily, then gradually increase to two or three times daily if needed or as directed by a doctor. If bothersome dryness or peeling occurs, reduce application to once a day or every other day.

Inactive Ingredient:

Water, Cyclopentasiloxane, Hydrogenated Polyisobutene, Ethoxydiglycol, Dimethicone, Cyclohexasiloxane, Dimethicone Crossploymer, PEG-10 Dimethicone, Dimethicone PEG 10/15 Crosspolymer, Magnesium Sulfate, Talc, Nylon-12, Phenoxyethanol, Propylene Glycol, Quaternium-18 Benonite, Triethoxycaprylysilane, Methylparaben, Ethylparaben, butylparaben, Propylparaben, Isobutylparaben, Cinnamomum Camphora (Camphor) Bark oil, Melaleuca Alternafolia (Tea Tree) Leaf Oil, Aloe Barbadensis Leaf Jiuce, Hexapeptide-9, Hamamelis Birginiana (Witch Hazel) May Contain: Iron Oxide (CI77491, CI77492, CI77499), Titanium Dioxide